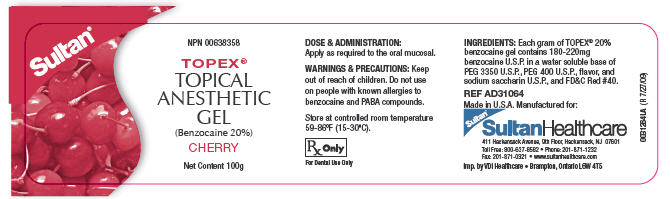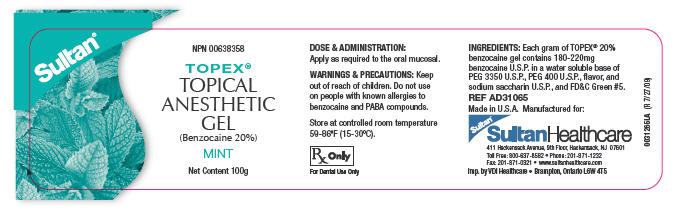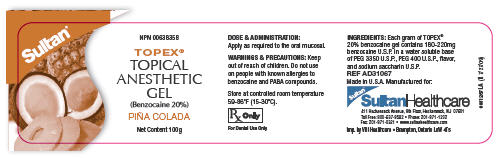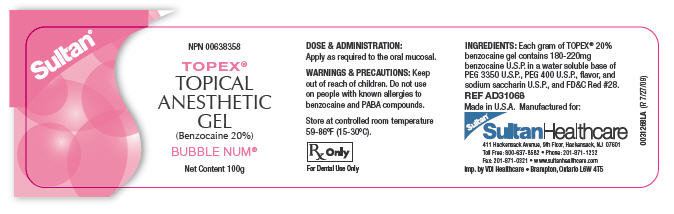 DRUG LABEL: Topex
NDC: 10216-3071 | Form: GEL, DENTIFRICE
Manufacturer: DENTSPLY Caulk
Category: prescription | Type: HUMAN PRESCRIPTION DRUG LABEL
Date: 20100204

ACTIVE INGREDIENTS: Benzocaine 220 mg/1 g

Topex® Topical Anesthetic Gel/Liquid –
20% Benzocaine

DIRECTIONS FOR USE

Gel – 1oz/30mL
REF AD31001 Cherry
REF AD31002 Mint
REF AD31003 Banana
REF AD31004 Pina Colada
REF AD31005 Bubble-Num
REF AD31006 Strawberry
REF AD31007 Razzberry

Gel – 100g jar
REF AD31064 Cherry
REF AD31964 Mint
REF AD31067 Pina Colada
REF AD31068 Bubble-Num

Liquid – 1oz/30mL
REF AD31011 Cherry
REF AD31012 Mint
REF AD31014 Pina Colada USP – 2oz/57g

NPN Number: 00638358
For dental use only.
USA: Rx only.

1. DESCRIPTION

Flavored 20% benzocaine gel or liquid for topical mucosal anesthesia.

2. INDICATIONS

Indicated as a topical anesthetic for use on oral mucosa prior to local anesthetic injections, scaling and prophylaxis. Also useful to relieve discomfort associated with taking impressions and intraoral radiographs.

3. CONTRAINDICATIONS

Should not be used with individuals with a known sensitivity to benzocaine or PABA.

4. WARNINGS

Keep out of reach of children. For professional dental use only.

5. PRECAUTIONS

Topex 20% benzocaine gels and liquids are supplied in multiple use containers. Take care not to contaminate the bottle by reintroducing a used cotton applicator into the bottle.

6. DOSAGE AND ADMINISTRATION

1. Each gram of Topex 20% benzocaine gel or liquid contains between 180-220mg benzocaine in a flavored base.
2. Using a new cotton applicator, apply a small amount of gel to the mucosa to achieve topical anesthesia. Do not reintroduce the cotton applicator into the bottle.
3. For topical tissue anesthesia during scaling procedures, dispense a small amount of Topex gel or liquid into a dappen dish, then coat the scaler with the product prior to use.
4. Tightly re-cap the jar after each use.

7. STORAGE

Store between 59°-86°F (15°-30°C). Protect from freezing.

SultanHealthcare
411 Hackensack Avenue, 9th Floor, Hackensack, NJ 07601
Toll Free: 800-637-8582 • Phone: 201-871-1232
Fax: 201-871-0321 • www.sultanhealthcare.com

Made in the USA
Form #0030502DF (R 7/22/09)

PRINCIPAL DISPLAY PANEL - 100 gram Jar Label

NPN 00638358

TOPEX®
TOPICAL
ANESTHETIC
GEL
(Benzocaine 20%)

CHERRY

Net Content 100g

PRINCIPAL DISPLAY PANEL - 100 gram Jar Label

NPN 00638358

TOPEX®
TOPICAL
ANESTHETIC
GEL
(Benzocaine 20%)

MINT

Net Content 100g

PRINCIPAL DISPLAY PANEL - 100 gram Jar Label

NPN 00638358

TOPEX®
TOPICAL
ANESTHETIC
GEL
(Benzocaine 20%)

PIÑA COLADA

Net Content 100g

PRINCIPAL DISPLAY PANEL - 100 gram Jar Label

NPN 00638358

TOPEX®
TOPICAL
ANESTHETIC
GEL
(Benzocaine 20%)

BUBBLE NUM®

Net Content 100g